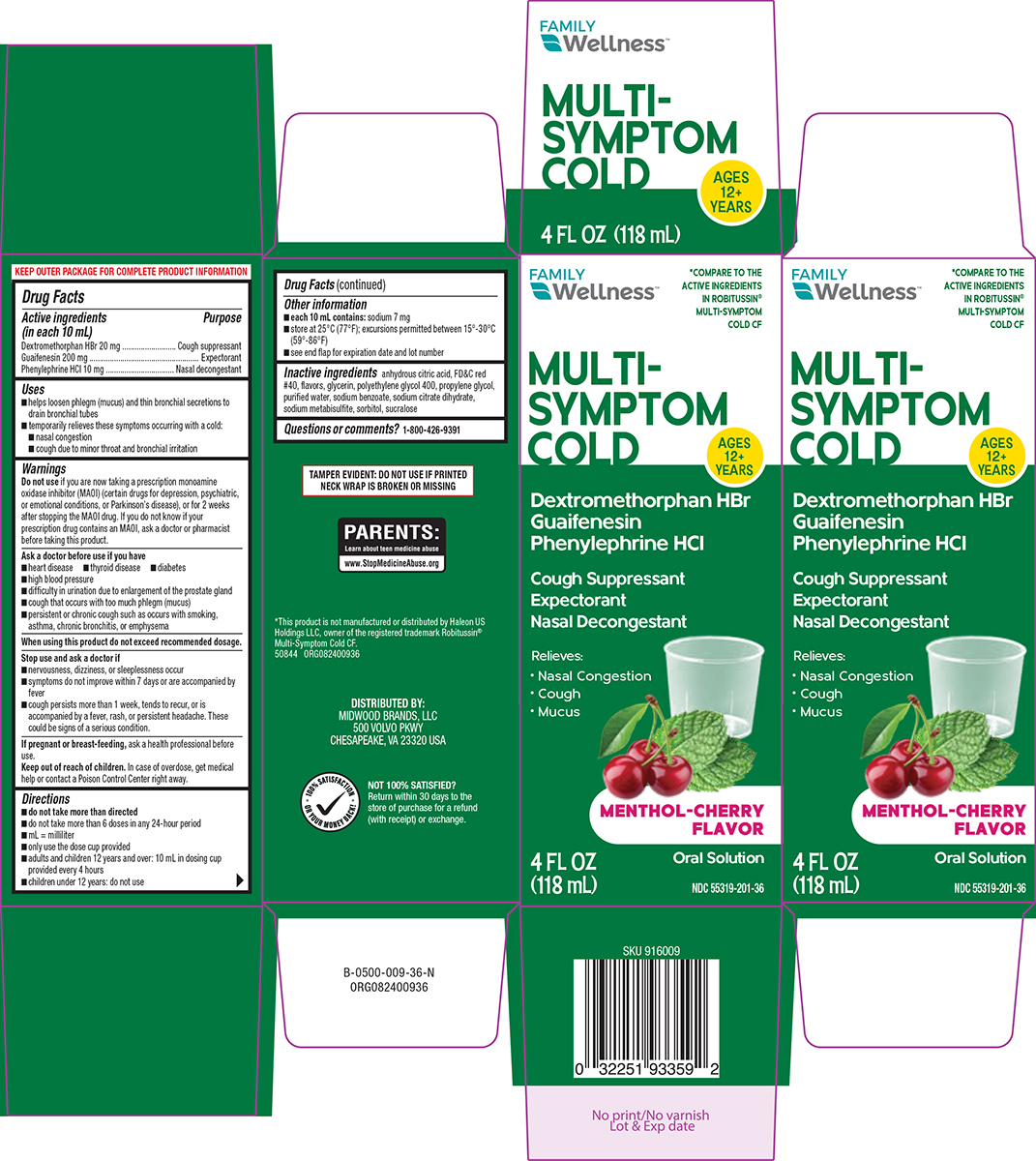 DRUG LABEL: MULTI-SYMPTOM COLD
NDC: 55319-201 | Form: SOLUTION
Manufacturer: Family Dollar Services Inc
Category: otc | Type: HUMAN OTC DRUG LABEL
Date: 20251115

ACTIVE INGREDIENTS: DEXTROMETHORPHAN HYDROBROMIDE 20 mg/10 mL; GUAIFENESIN 200 mg/10 mL; PHENYLEPHRINE HYDROCHLORIDE 10 mg/10 mL
INACTIVE INGREDIENTS: ANHYDROUS CITRIC ACID; FD&C RED NO. 40; GLYCERIN; POLYETHYLENE GLYCOL 400; PROPYLENE GLYCOL; WATER; SODIUM BENZOATE; TRISODIUM CITRATE DIHYDRATE; SODIUM METABISULFITE; SORBITOL; SUCRALOSE

Family Wellness 44-009

Active ingredients (in each 10 mL)

Dextromethorphan HBr 20 mg
Guaifenesin 200 mg
Phenylephrine HCl 10 mg

Purpose

Cough suppressant
Expectorant
Nasal decongestant

Uses

- helps loosen phlegm (mucus) and thin bronchial secretions to drain bronchial tubes
- temporarily relieves these symptoms occurring with a cold:
  - nasal congestion
  - cough due to minor throat and bronchial irritation

Warnings

Do not use

if you are now taking a prescription monoamine oxidase inhibitor (MAOI) (certain drugs for depression, psychiatric, or emotional conditions, or Parkinson’s disease), or for 2 weeks after stopping the MAOI drug. If you do not know if your prescription drug contains an MAOI, ask a doctor or pharmacist before taking this product.

Ask a doctor before use if you have

- heart disease
- thyroid disease
- diabetes
- high blood pressure
- difficulty in urination due to enlargement of the prostate gland
- cough that occurs with too much phlegm (mucus)
- persistent or chronic cough such as occurs with smoking, asthma, chronic bronchitis, or emphysema

When using this product

do not exceed recommended dosage.

Stop use and ask a doctor if

- nervousness, dizziness, or sleeplessness occur
- symptoms do not improve within 7 days or are accompanied by fever
- cough persists more than 1 week, tends to recur, or is accompanied by a fever, rash, or persistent headache. These could be signs of a serious condition.

If pregnant or breast-feeding,

ask a health professional before use.

Keep out of reach of children.

In case of overdose, get medical help or contact a Poison Control Center right away.

Directions

- do not take more than directed
- do not take more than 6 doses in any 24-hour period
- mL = milliliter
- only use the dose cup provided
- adults and children 12 years and over: 10 mL in dosing cup provided every 4 hours
- children under 12 years: do not use

Other information

- each 10 mL contains: sodium 7 mg
- store at 25°C (77°F); excursions permitted between 15°-30°C (59°-86°F)
- see end flap for expiration date and lot number

Inactive ingredients

anhydrous citric acid, FD&C red #40, flavors, glycerin, polyethylene glycol 400, propylene glycol, purified water, sodium benzoate, sodium citrate dihydrate, sodium metabisulfite, sorbitol, sucralose

Questions or comments?

1-800-426-9391

Principal display panel

FAMILY
Wellness™

*COMPARE TO THE
ACTIVE INGREDIENTS
IN ROBITUSSIN®
MULTI-SYMPTOM
COLD CF

MULTI-
SYMPTOM
COLD

Dextromethorphan HBr
Guaifenesin
Phenylephrine HCl

Cough Suppressant
Expectorant
Nasal Decongestant

Relieves:
• Nasal Congestion
• Cough
• Mucus

MENTHOL-CHERRY
FLAVOR

AGES
12+
YEARS

Oral Solution

NDC 55319-201-36

4 FL OZ
(118 mL)

TAMPER EVIDENT: DO NOT USE IF PRINTED
NECK WRAP IS BROKEN OR MISSING

PARENTS:
Learn about teen medicine abuse
www.StopMedicineAbuse.org

*This product is not manufactured or distributed by Haleon US
Holdings LLC, owner of the registered trademark Robitussin®
Multi-Symptom Cold CF.
50844 ORG082400936

DISTRIBUTED BY:
MIDWOOD BRANDS, LLC
500 VOLVO PKWY
CHESAPEAKE, VA 23320 USA

NOT 100% SATISFIED?
Return within 30 days to the
store of purchase for a refund
(with receipt) or exchange.

100% SATISFACTION
✓
• OR YOUR MONEY BACK! •

Family Wellness 44-009